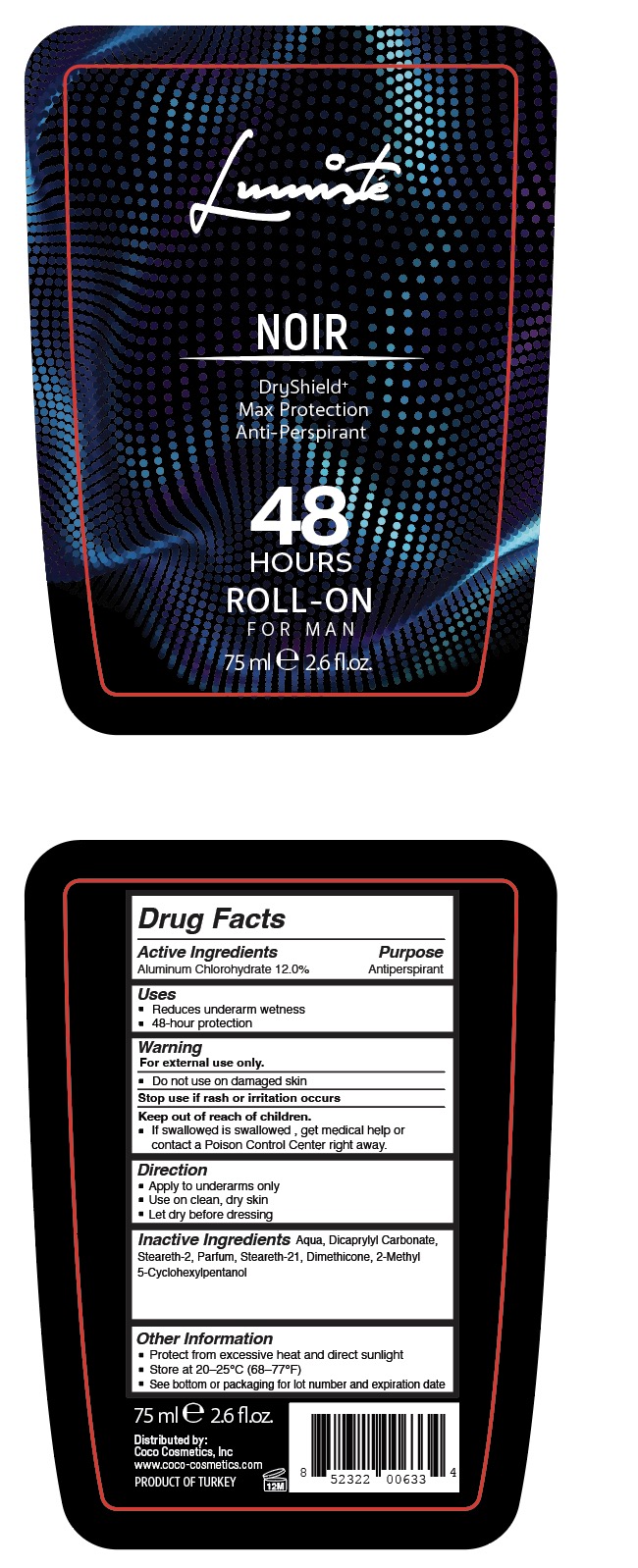 DRUG LABEL: LUMISTE NOIR BLACK
NDC: 87093-115 | Form: LIQUID
Manufacturer: COCO COSMETICS INC
Category: otc | Type: HUMAN OTC DRUG LABEL
Date: 20251109

ACTIVE INGREDIENTS: ALUMINUM CHLOROHYDRATE 12 mg/100 mL
INACTIVE INGREDIENTS: DICAPRYLYL CARBONATE; DIMETHICONE; LEMON; STEARETH-2; STEARETH-21; 2-METHYL 5-CYCLOHEXYLPENTANOL; WATER

COCO- ATAK LUMISTE NOIR BLACK

Active Ingredient(s)

Aluminum Chlorohydrate 12.0%

Purpose

Antiperspirant

Use

Reduces underarm wetness

48-hour protection

Warnings

For external use only.

Do not use on damaged skin.

Stop use if rash or irritation occurs

Keep out of reach of children.

If swallowed, get medical help or contact a Poison Control Center right away.

Directions

• Apply to underarms only

• Use on clean, dry skin

• Let dry before dressing

Other information

• Protect from excessive heat and direct sunlight

• Store at 20-250C (68-770F)

• See bottom of packaging for lot number and expiration date

Inactive ingredients

Aqua, Dicaprylyl Carbonate,

Steareth-2, Parfum, Steareth-21 , Dimethicone, 2-Methyl

5-Cyclohexylpentanol